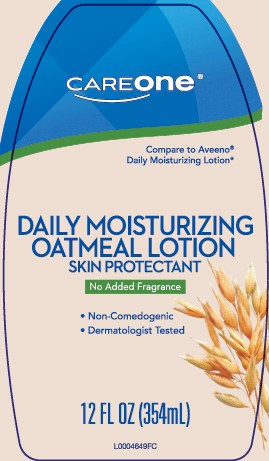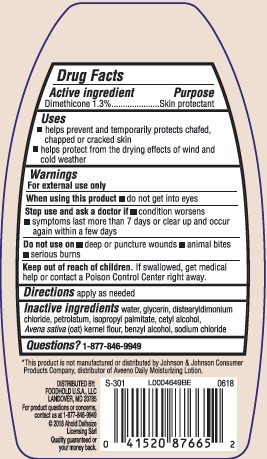 DRUG LABEL: Daily Moisturizing
NDC: 72476-619 | Form: LOTION
Manufacturer: Retail Business Services, LLC
Category: otc | Type: HUMAN OTC DRUG LABEL
Date: 20260206

ACTIVE INGREDIENTS: DIMETHICONE 13 mg/1 mL
INACTIVE INGREDIENTS: WATER; GLYCERIN; DISTEARYLDIMONIUM CHLORIDE; PETROLATUM; ISOPROPYL PALMITATE; CETYL ALCOHOL; OATMEAL; BENZYL ALCOHOL; SODIUM CHLORIDE

Care One 619.003/619AC rev 2
Daily Moisturizing Lotion

Active ingredient

Dimethicone 1.3%

Purpose

Skin protectant

Uses

- helps prevent and temporarily protects chafed, chapped or cracked skin
- helps protect from the drying effects of wind and cold weather

Warnings

For external use only

When using this product

- do not get into eyes

Stop use aned ask a doctor if

- condition worsens
- symptoms last more than 7 days or clear up and occur again within a few days

Do not use on

- deep or punture wounds
- animal bites
- serious burns

Keep out of reach of children

If swallowed, get medical help or contact a Poison Control Center right away.

Directions

apply as needed

Inactive ingredients

water, glycerin, distearyldimonium chloride, petrolatum, isopropyl palmitate, cetyl alcohol, Avena sativa (oat) kernel flour, benzyl alcohol, sodium chloride

Disclaimer

*This product is not manufactured or distributed by Johnson & Johnson Consumer Products Company, distributor of Aveeno Daily Moisturizing Lotion.

Adverse Reactions

DISTRIBUTED BY:

FOODHOLD U.S.A., LLC

LANDOVER, MD 20785

For product questions or concerns, contact us at 1-877-846-9949

2018 Ahold Delhaize Licensing Sarl

QUALITY GUARANTEED OR YOUR MONEY BACK.

principal display panel

CAREONE®

Compare to Aveeno®Daily Moisturizing Lotion*

Daily Moisturizing

Oatmeal Lotion

Skin Protectant

No Added Fragrance

- Non-Comedogenic
- Dermatologist Tested

12 FL OZ (354 mL)